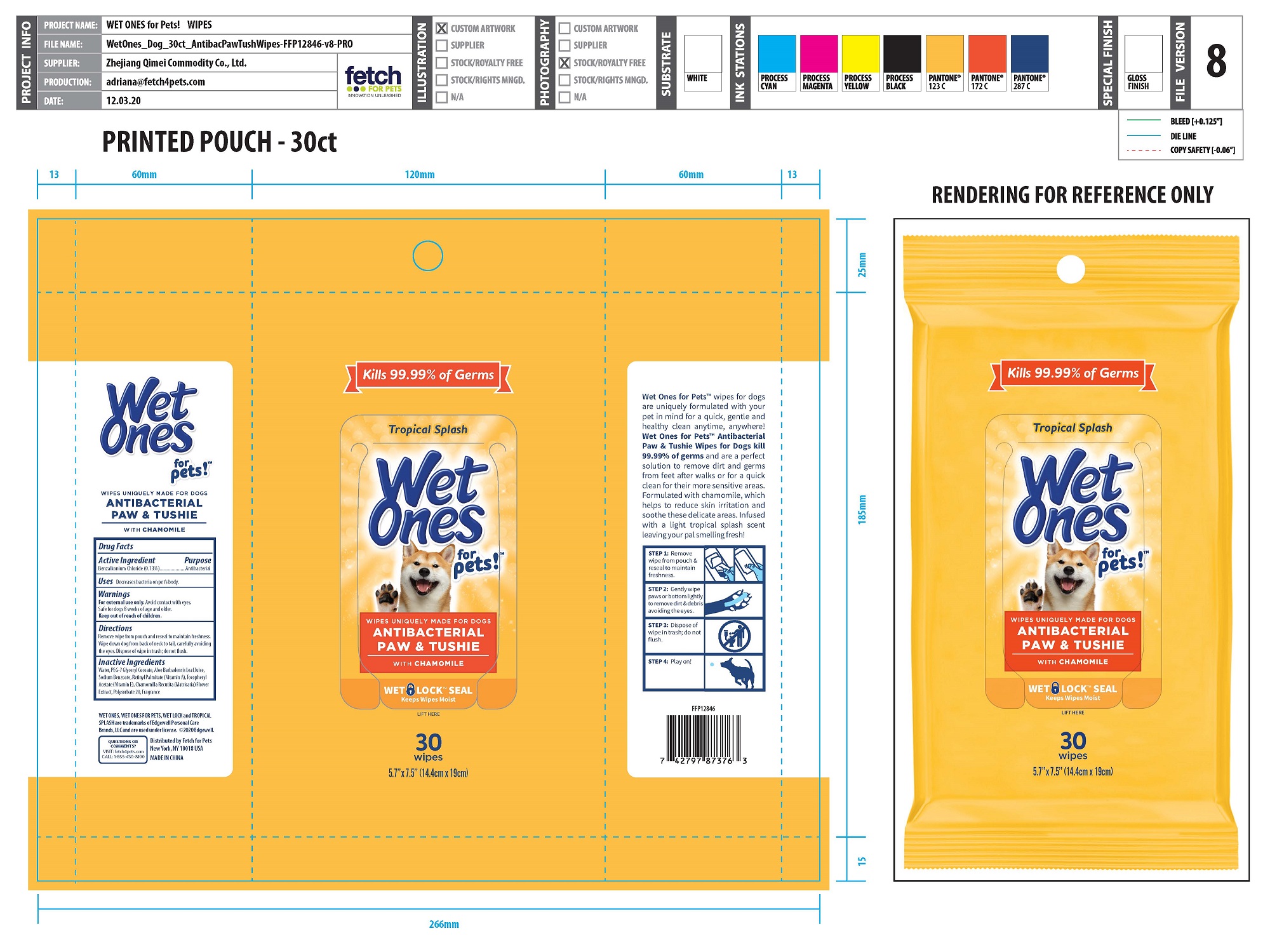 DRUG LABEL: Antibacterial Paw Tushie wipes
NDC: 77720-026 | Form: CLOTH
Manufacturer: Skaffles Group Limited Liability Company
Category: animal | Type: OTC ANIMAL DRUG LABEL
Date: 20210224

ACTIVE INGREDIENTS: BENZALKONIUM CHLORIDE 0.13 g/100 g
INACTIVE INGREDIENTS: WATER; VITAMIN A PALMITATE; .ALPHA.-TOCOPHEROL ACETATE; ALOE VERA LEAF; POLYSORBATE 20; CHAMOMILE; SODIUM BENZOATE; PEG-7 GLYCERYL COCOATE

Active Ingredient

Benzalkonium Chloride 0.13%

Purpose

Antibacterial

USE

Decreases Bacteria on pet]s body.

Warning

For external use only.

Avoid Contact with eyes. Safe for dogs 8 weeks of age and older.

Keep out of reach of children.

Directions

Remove wipe from pouch and reseal to maintain freshness.Wipe down dog from back ofneck to tail, carefully avoiding the eyes. Dispose of wipe in trash; do not flush.

Inactive ingredients

Water, PEG-7 Glyceryl Cocoate,Aloe Barbadensis LeafJuice,Sodium Benzoate, RetinylPalmitate (Vitamin A), TocopherylAcetate (Mitamin E), Chamomilla Recutita (Matricaria) FlowerExtract, Polysorbate 20,Fragrance